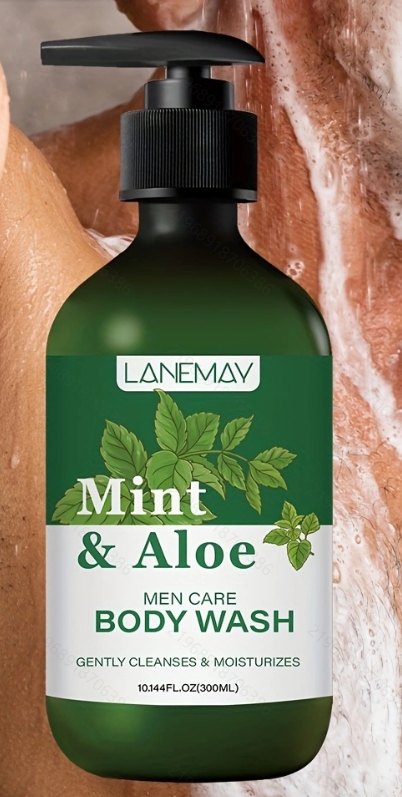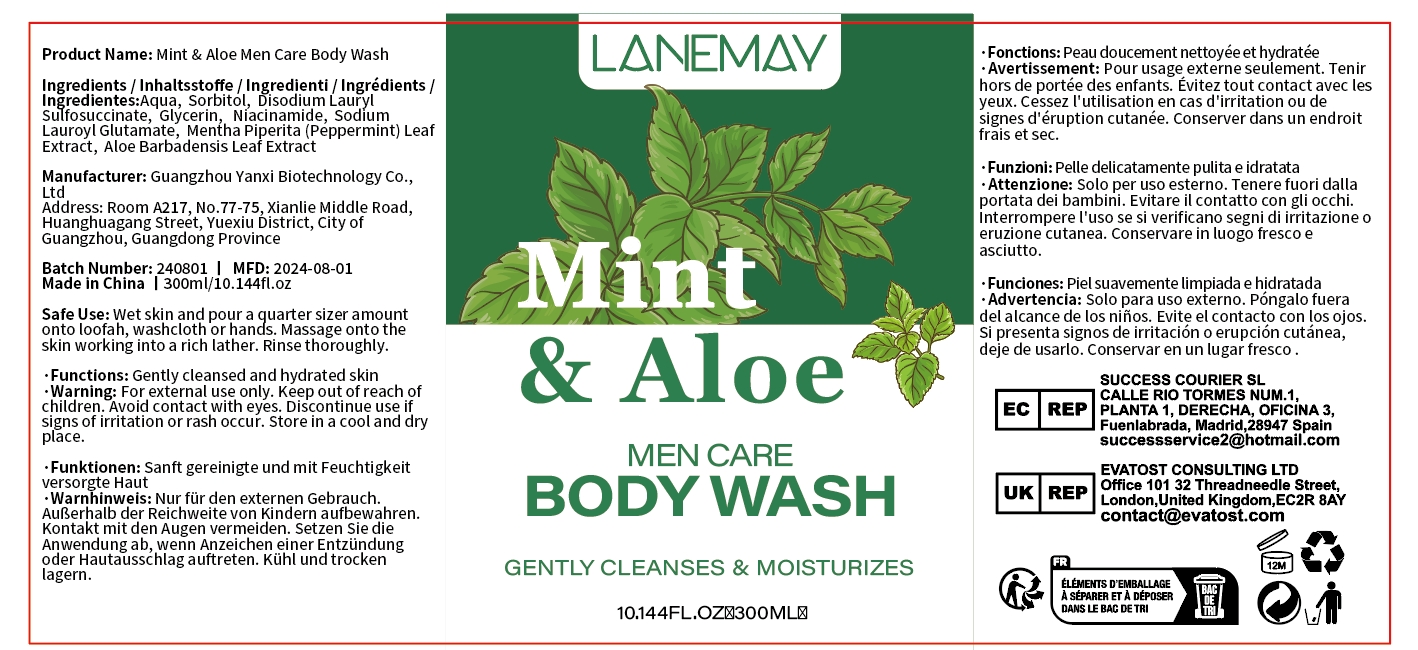 DRUG LABEL: Mint  Aloe Men Care Body Wash
NDC: 84025-262 | Form: CREAM
Manufacturer: Guangzhou Yanxi Biotechnology Co., Ltd
Category: otc | Type: HUMAN OTC DRUG LABEL
Date: 20241115

ACTIVE INGREDIENTS: NIACINAMIDE 13 mg/300 mL; SORBITOL 15 mg/300 mL
INACTIVE INGREDIENTS: WATER

DOSAGE AND ADMINISTRATION

Wet skin and pour a quarter sizer amount onto loofah,washcloth or hands.Massage onto the skin working into a rich lather. Rinse thoroughly.

WARNINGS

Keep out of children

INACTIVE INGREDIENT

Aqua

INDICATIONS AND USAGE

For daily skin clean

Keep out of children

PURPOSE

Cleanses and moisturizes skin